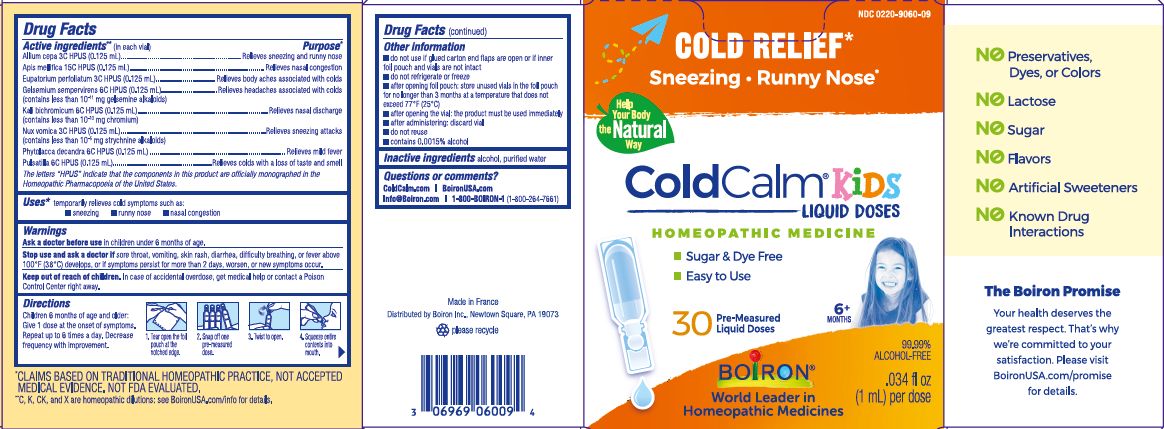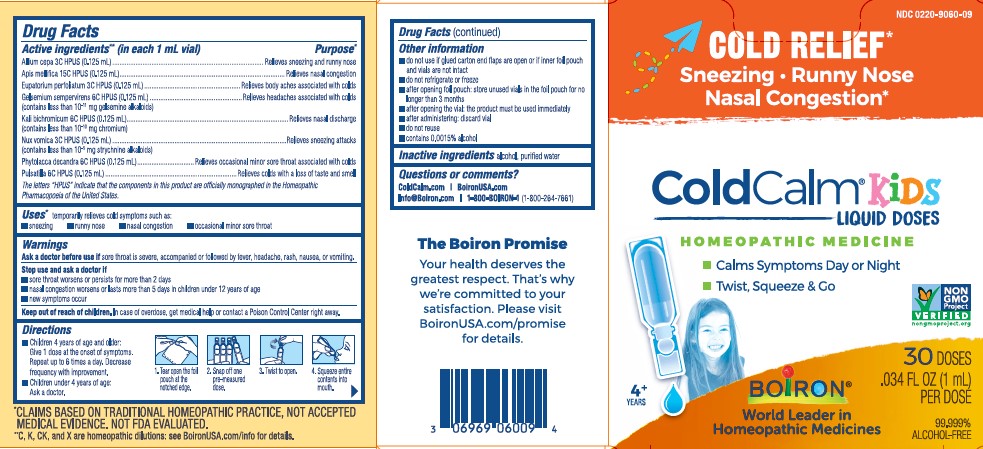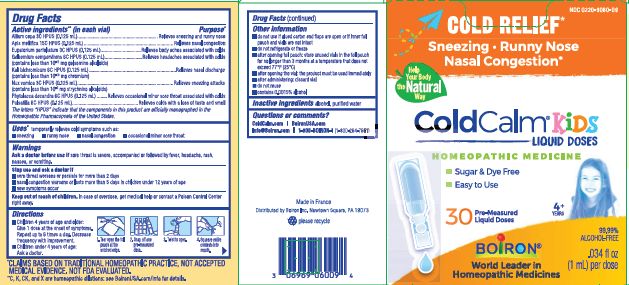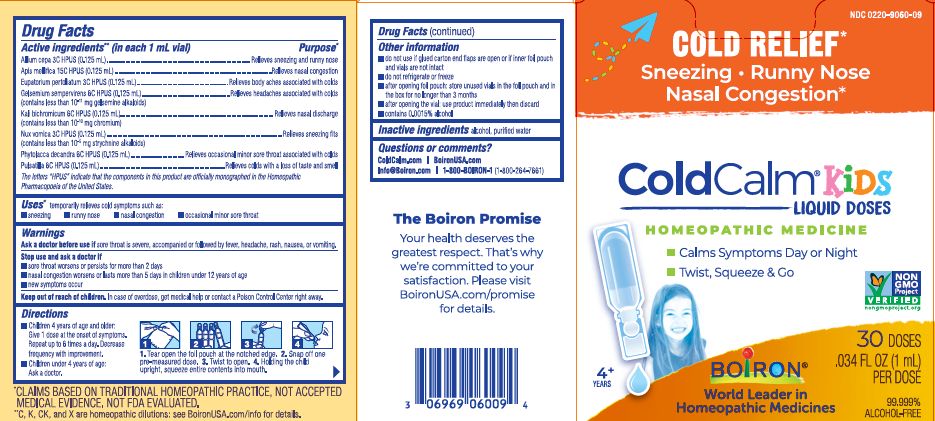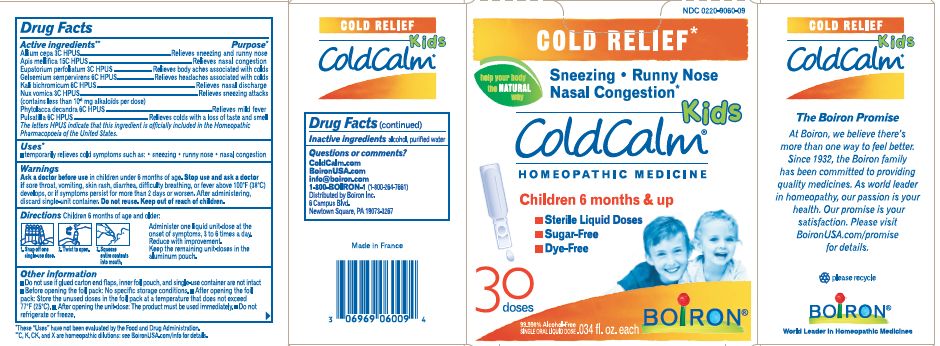 DRUG LABEL: ColdCalm Kids
NDC: 0220-9060 | Form: LIQUID
Manufacturer: Boiron
Category: homeopathic | Type: HUMAN OTC DRUG LABEL
Date: 20250902

ACTIVE INGREDIENTS: STRYCHNOS NUX-VOMICA SEED 3 [hp_C]/1 1; PULSATILLA VULGARIS 6 [hp_C]/1 1; ONION 3 [hp_C]/1 1; APIS MELLIFERA 15 [hp_C]/1 1; EUPATORIUM PERFOLIATUM FLOWERING TOP 3 [hp_C]/1 1; GELSEMIUM SEMPERVIRENS ROOT 6 [hp_C]/1 1; POTASSIUM DICHROMATE 6 [hp_C]/1 1; PHYTOLACCA AMERICANA ROOT 6 [hp_C]/1 1
INACTIVE INGREDIENTS: ALCOHOL; WATER

ColdCalm Kids Liquid

Active ingredients** (in each 1 mL vial)

Allium cepa 3C HPUS (0.125 mL)

Apis mellifica 15C HPUS (0.125 mL)

Eupatorium perfoliatum 3C HPUS (0.125 mL)

Gelsemium sempervirens 6C HPUS (0.125 mL) (contains less than 10^-11 mg gelsemine alkaloids)

Kali bichromicum 6C HPUS (0.125 mL) (contains less than 10^-10 mg chromium)

Nux vomica 3C HPUS (0.125 mL) (contains less than 10^-5 strychnine alkaloids)

Phytolacca decandra 6C HPUS (0.125 mL)

Pulsatilla 6C HPUS (0.125 mL)

The letters "HPUS" indicate that the components in this product are officially monographed in the Homeopathic Pharmacopoeia of the United States.

Purpose*

Allium cepa 3C HPUS (0.125 mL) ... Relieves sneezing and runny nose

Apis mellifica 15C HPUS (0.125 mL) ... Relieves nasal congestion

Eupatorium perfoliatum 3C HPUS (0.125 mL) ... Relieves body aches associated with colds

Gelsemium sempervirens 6C HPUS (0.125 mL) ...Relieves headaches associated with colds

Kali bichromicum 6C HPUS (0.125 mL) ... Relieves nasal discharge

Nux vomica 3C HPUS (0.125 mL) ... Relieves sneezing attacks

Phytolacca decandra 6C HPUS (0.125 mL) ... Relieves occasional minor sore throat associated with colds

Pulsatilla 6C HPUS (0.125 mL) ... Relieves colds with a loss of taste and smell

Uses*

Temporarily relieves cold symptoms such as:

- sneezing
- runny nose
- nasal congestion
- occasional minor sore throat

Ask a doctor before use if sore throat is severe, accompanied or follow by fever, headache, rash, nausea, or vomiting.

Stop use and ask a doctor if

- sore throat worsens or persists for more than 2 days
- nasal congestion worsens or lasts more than 5 days in children under 12 years of age
- new symptoms occur

Keep out of reach of children. In case of overdose, get medical help or contact a Poison Control Center right away.

DOSAGE AND ADMINISTRATION

Children 4 years of age and older: Give 1 dose at the onset of symptoms. Repeat up to 6 times a day. Decrease frequency with improvement.

Children under 4 years of age: Ask a doctor.

1. Tear open the foil pouch at the notched edge.
2. Snap off pre-measured dose.
3. Twist to open.
4. Holding the child upright, squeeze entire contents into mouth.

- do not use if glued carton end flaps are open or if inner foil pouch and vials are not intact
- do not refrigerate or freeze
- after opening foil pouch: store unused vials in the foil pouch and in the box for no longer than 3 months
- after opening the vial: use product immediately then discard
- contains 0.0015% alcohol

30 Doses

.034 fl oz (1 mL) per dose

No Known Drug Interactions

Cold Relief*

Sneezy, Runny Nose, Nasal Congestion*

*CLAIMS BASED ON TRADITIONAL HOMEOPATHIC PRACTICE NOT ACCEPTED MEDICAL EVIDENCE. NOT FDA EVALUATED.
**C,K,CK, and X are homeopathic dilutions: see BoironUSA.com/info for details.

INACTIVE INGREDIENT

alcohol, purified water

QUESTIONS

ColdCalm.com
BoironUSA.com
info@boiron.com
1-800-BOIRON-1 (1-800-264-7661)
Distributed by Boiron Inc. Newtown Square, PA 19073-3267